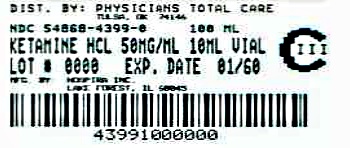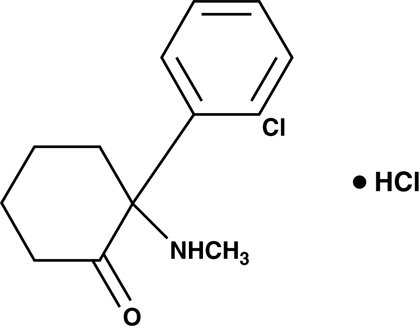 DRUG LABEL: Ketamine Hydrochloride
NDC: 54868-4399 | Form: INJECTION, SOLUTION, CONCENTRATE
Manufacturer: Physicians Total Care, Inc.
Category: prescription | Type: HUMAN PRESCRIPTION DRUG LABEL
Date: 20120423
DEA Schedule: CIII

ACTIVE INGREDIENTS: KETAMINE HYDROCHLORIDE 50 mg/1 mL
INACTIVE INGREDIENTS: BENZETHONIUM CHLORIDE 0.1 mg/1 mL

Ketamine
Hydrochloride
Injection, USP

CIII

Rx only

SPECIAL NOTE

EMERGENCE REACTIONS HAVE OCCURRED IN APPROXIMATELY 12 PERCENT OF PATIENTS.

THE PSYCHOLOGICAL MANIFESTATIONS VARY IN SEVERITY BETWEEN PLEASANT DREAM-LIKE STATES, VIVID IMAGERY, HALLUCINATIONS, AND EMERGENCE DELIRIUM. IN SOME CASES THESE STATES HAVE BEEN ACCOMPANIED BY CONFUSION, EXCITEMENT, AND IRRATIONAL BEHAVIOR WHICH A FEW PATIENTS RECALL AS AN UNPLEASANT EXPERIENCE. THE DURATION ORDINARILY IS NO MORE THAN A FEW HOURS; IN A FEW CASES, HOWEVER, RECURRENCES HAVE TAKEN PLACE UP TO 24 HOURS POSTOPERATIVELY. NO RESIDUAL PSYCHOLOGICAL EFFECTS ARE KNOWN TO HAVE RESULTED FROM USE OF KETAMINE.

THE INCIDENCE OF THESE EMERGENCE PHENOMENA IS LEAST IN THE ELDERLY (OVER 65 YEARS OF AGE) PATIENT. ALSO, THEY ARE LESS FREQUENT WHEN THE DRUG IS GIVEN INTRAMUSCULARLY AND THE INCIDENCE IS REDUCED AS EXPERIENCE WITH THE DRUG IS GAINED.

THE INCIDENCE OF PSYCHOLOGICAL MANIFESTATIONS DURING EMERGENCE, PARTICULARLY DREAM-LIKE OBSERVATIONS AND EMERGENCE DELIRIUM, MAY BE REDUCED BY USING LOWER RECOMMENDED DOSAGES OF KETAMINE IN CONJUNCTION WITH INTRAVENOUS DIAZEPAM DURING INDUCTION AND MAINTENANCE OF ANESTHESIA. (See DOSAGE AND ADMINISTRATION.) ALSO, THESE REACTIONS MAY BE REDUCED IF VERBAL, TACTILE AND VISUAL STIMULATION OF THE PATIENT IS MINIMIZED DURING THE RECOVERY PERIOD. THIS DOES NOT PRECLUDE THE MONITORING OF VITAL SIGNS.

IN ORDER TO TERMINATE A SEVERE EMERGENCE REACTION THE USE OF A SMALL HYPNOTIC DOSE OF A SHORT-ACTING OR ULTRASHORT-ACTING BARBITURATE MAY BE REQUIRED.

WHEN KETAMINE IS USED ON AN OUTPATIENT BASIS, THE PATIENT SHOULD NOT BE RELEASED UNTIL RECOVERY FROM ANESTHESIA IS COMPLETE AND THEN SHOULD BE ACCOMPANIED BY A RESPONSIBLE ADULT.

DESCRIPTION

Ketamine hydrochloride is a nonbarbiturate anesthetic chemically designated (±)-2-(o-Chlorophenyl)-2-(methylamino) cyclohexanone hydrochloride. It is formulated as a slightly acid (pH 3.5 to 5.5) sterile solution for intravenous or intramuscular injection in concentrations containing the equivalent of either 50 or 100 mg ketamine base per milliliter and contains not more than 0.1 mg/mL benzethonium chloride added as a preservative. Ketamine hydrochloride has a molecular formula of C13H16ClNO• HCl, a molecular weight of 274.19 and the following structural formula:

CLINICAL PHARMACOLOGY

Ketamine is a rapid-acting general anesthetic producing an anesthetic state characterized by profound analgesia, normal pharyngeal-laryngeal reflexes, normal or slightly enhanced skeletal muscle tone, cardiovascular and respiratory stimulation, and occasionally a transient and minimal respiratory depression.

A patent airway is maintained partly by virtue of unimpaired pharyngeal and laryngeal reflexes. (See WARNINGS and PRECAUTIONS.)

The biotransformation of ketamine includes N-dealkylation (metabolite I), hydroxylation of the cyclohexone ring (metabolites III and IV), conjugation with glucuronic acid and dehydration of the hydroxylated metabolites to form the cyclohexene derivative (metabolite II).

Following intravenous administration, the ketamine concentration has an initial slope (alpha phase) lasting about 45 minutes with a half-life of 10 to 15 minutes. This first phase corresponds clinically to the anesthetic effect of the drug. The anesthetic action is terminated by a combination of redistribution from the CNS to slower equilibrating peripheral tissues and by hepatic biotransformation to metabolite I. This metabolite is about 1/3 as active as ketamine in reducing halothane requirements (MAC) of the rat. The later half-life of ketamine (beta phase) is 2.5 hours.

The anesthetic state produced by ketamine has been termed “dissociative anesthesia” in that it appears to selectively interrupt association pathways of the brain before producing somesthetic sensory blockade. It may selectively depress the thalamoneocortical system before significantly obtunding the more ancient cerebral centers and pathways (reticular-activating and limbic systems).

Elevation of blood pressure begins shortly after injection, reaches a maximum within a few minutes and usually returns to preanesthetic values within 15 minutes after injection. In the majority of cases, the systolic and diastolic blood pressure peaks from 10% to 50% above preanesthetic levels shortly after induction of anesthesia, but the elevation can be higher or longer in individual cases (see CONTRAINDICATIONS).

Ketamine has a wide margin of safety; several instances of unintentional administration of overdoses of ketamine (up to ten times that usually required) have been followed by prolonged butcomplete recovery.

Ketamine has been studied in over 12,000 operative and diagnostic procedures, involving over 10,000 patients from 105 separate studies. During the course of these studies ketamine hydrochloride was administered as the sole agent, as induction for other general agents, or to supplement low-potency agents.

Specific areas of application have included the following:

1. debridement, painful dressings, and skin grafting in burn patients, as well as other superficial surgical procedures.
2. neurodiagnostic procedures such as pneumonencephalograms, ventriculograms, myelograms, and lumbar punctures. See also PRECAUTION concerning increased intracranial pressure.
3. diagnostic and operative procedures of the eye, ear, nose, and mouth, including dental extractions.
4. diagnostic and operative procedures of the pharynx, larynx, or bronchial tree. NOTE: Muscle relaxants, with proper attention to respiration, may be required (see PRECAUTIONS section).
5. sigmoidoscopy and minor surgery of the anus and rectum, and circumcision.
6. extraperitoneal procedures used in gynecology such as dilatation and curettage.
7. orthopedic procedures such as closed reductions, manipulations, femoral pinning, amputations, and biopsies.
8. as an anesthetic in poor-risk patients with depression of vital functions.
9. in procedures where the intramuscular route of administration is preferred.
10. in cardiac catheterization procedures.

In these studies, the anesthesia was rated either “excellent” or “good” by the anesthesiologist and the surgeon at 90% and 93%, respectively; rated “fair” at 6% and 4%, respectively; and rated “poor” at 4% and 3%, respectively. In a second method of evaluation, the anesthesia was rated “adequate” in at least 90% and “inadequate” in 10% or less of the procedures.

INDICATIONS AND USAGE

Ketamine hydrochloride injection is indicated as the sole anesthetic agent for diagnostic and surgical procedures that do not require skeletal muscle relaxation. Ketamine hydrochloride injection is best suited for short procedures but it can be used, with additional doses, for longer procedures.

Ketamine hydrochloride injection is indicated for the induction of anesthesia prior to the administration of other general anesthetic agents.

Ketamine hydrochloride injection is indicated to supplement low-potency agents, such as nitrous oxide.

Specific areas of application are described in the CLINICAL PHARMACOLOGY section.

CONTRAINDICATIONS

Ketamine is contraindicated in those in whom a significant elevation of blood pressure would constitute a serious hazard and in those who have shown hypersensitivity to the drug.

WARNINGS

Cardiac function should be continually monitored during the procedure in patients found to have hypertension or cardiac decompensation.

Postoperative confusional states may occur during the recovery period. (See SPECIAL NOTE.)

Respiratory depression may occur with overdosage or too rapid a rate of administration of ketamine, in which case supportive ventilation should be employed. Mechanical support of respiration is preferred to administration of analeptics.

PRECAUTIONS

General

Ketamine should be used by or under the direction of physicians experienced in administering general anesthetics and in maintenance of an airway and in the control of respiration.

Because pharyngeal and laryngeal reflexes are usually active, ketamine should not be used alone in surgery or diagnostic procedures of the pharynx, larynx, or bronchial tree. Mechanical stimulation of the pharynx should be avoided, whenever possible, if ketamine is used alone. Muscle relaxants, with proper attention to respiration, may be required in both of these instances.

Resuscitative equipment should be ready for use.

The incidence of emergence reactions may be reduced if verbal and tactile stimulation of the patient is minimized during the recovery period. This does not preclude the monitoring of vital signs (see SPECIAL NOTE).

The intravenous dose should be administered over a period of 60 seconds. More rapid administration may result in respiratory depression or apnea and enhanced pressor response.

In surgical procedures involving visceral pain pathways, ketamine should be supplemented with an agent which obtunds visceral pain.

Use with caution in the chronic alcoholic and the acutely alcohol-intoxicated patient.

An increase in cerebrospinal fluid pressure has been reported following administration of ketamine. Use with extreme caution in patients with preanesthetic elevated cerebrospinal fluid pressure.

Information for Patients

As appropriate, especially in cases where early discharge is possible, the duration of ketamine and other drugs employed during the conduct of anesthesia should be considered. The patients should be cautioned that driving an automobile, operating hazardous machinery or engaging in hazardous activities should not be undertaken for 24 hours or more (depending upon the dosage of ketamine and consideration of other drugs employed) after anesthesia.

Drug Interactions

Prolonged recovery time may occur if barbiturates and/or narcotics are used concurrently with ketamine.

Ketamine is clinically compatible with the commonly used general and local anesthetic agents when an adequate respiratory exchange is maintained.

Usage in Pregnancy

Since the safe use in pregnancy, including obstetrics (either vaginal or abdominal delivery), has not been established, such use is not recommended (see ANIMAL PHARMACOLOGY AND TOXICOLOGY, Reproduction).

Geriatric Use

Clinical studies of ketamine hydrochloride did not include sufficient numbers of subjects aged 65 and over to determine whether they respond differently from younger subjects. Other reported clinical experience has not identified differences in responses between the elderly and younger patients. In general, dose selection for an elderly patient should be cautious, usually starting at the low end of the dosing range, reflecting the greater frequency of decreased hepatic, renal, or cardiac function, and of concomitant disease or other drug therapy.

Pediatric Use

Safety and effectiveness in pediatric patients below the age of 16 have not been established.

ADVERSE REACTIONS

Cardiovascular

Blood pressure and pulse rate are frequently elevated following administration of ketamine alone. However, hypotension and bradycardia have been observed. Arrhythmia has also occurred.

Respiration

Although respiration is frequently stimulated, severe depression of respiration or apnea may occur following rapid intravenous administration of high doses of ketamine. Laryngospasms and other forms of airway obstruction have occurred during ketamine anesthesia.

Eye

Diplopia and nystagmus have been noted following ketamine administration. It also may cause a slight elevation in intraocular pressure measurement.

Psychological: (See SPECIAL NOTE.)

Neurological

In some patients, enhanced skeletal muscle tone may be manifested by tonic and clonic movements sometimes resembling seizures (see DOSAGE AND ADMINISTRATION section).

Gastrointestinal

Anorexia, nausea and vomiting have been observed; however, this is not usually severe and allows the great majority of patients to take liquids by mouth shortly after regaining consciousness (see DOSAGE AND ADMINISTRATION section).

General: Anaphylaxis

Local pain and exanthema at the injection site have infrequently been reported. Transient erythema and/or morbilliform rash have also been reported.

DRUG ABUSE AND DEPENDENCE

Ketamine has been reported being used as a drug of abuse. Reports suggest that ketamine produces a variety of symptoms including, but not limited to anxiety, dysphoria, disorientation, insomnia, flashbacks, hallucinations, and psychotic episodes. Ketamine dependence and tolerance are possible following prolonged administration. A withdrawal syndrome with psychotic features has been described following discontinuation of long-term ketamine use. Therefore, ketamine should be prescribed and administered with caution.

OVERDOSAGE

Respiratory depression may occur with overdosage or too rapid a rate of administration of ketamine, in which case supportive ventilation should be employed. Mechanical support of respiration is preferred to administration of analeptics.

DOSAGE AND ADMINISTRATION

Parenteral drug products should be inspected visually for particulate matter and discoloration prior to administration, whenever solution and container permit.

Note: Barbiturates and ketamine, being chemically incompatible because of precipitate formation, should not be injected from the same syringe.

If the ketamine dose is augmented with diazepam, the two drugs must be given separately. Do not mix ketamine hydrochloride and diazepam in syringe or infusion flask. For additional information on the use of diazepam, refer to the WARNINGS and DOSAGE AND ADMINISTRATION sections of the diazepam insert.

Preoperative Preparations

1. While vomiting has been reported following ketamine administration, some airway protection may be afforded because of active laryngeal-pharyngeal reflexes. However, since aspiration may occur with ketamine and since protective reflexes may also be diminished by supplementary anesthetics and muscle relaxants, the possibility of aspiration must be considered. Ketamine is recommended for use in the patient whose stomach is not empty when, in the judgment of the practitioner, the benefits of the drug outweigh the possible risks.
2. Atropine, scopolamine, or another drying agent should be given at an appropriate interval prior to induction.

Onset and Duration

Because of rapid induction following the initial intravenous injection, the patient should be in a supported position during administration.

The onset of action of ketamine is rapid; an intravenous dose of 2 mg/kg (1 mg/lb) of body weight usually produces surgical anesthesia within 30 seconds after injection, with the anesthetic effect usually lasting five to ten minutes. If a longer effect is desired, additional increments can be administered intravenously or intramuscularly to maintain anesthesia without producing significant cumulative effects.

Intramuscular doses, in a range of 9 to13 mg/kg (4 to 6 mg/lb) usually produce surgical anesthesia within 3 to 4 minutes following injection, with the anesthetic effect usually lasting 12 to 25 minutes.

Dosage

As with other general anesthetic agents, the individual response to ketamine is somewhat varied depending on the dose, route of administration, and age of patient, so that dosage recommendation cannot be absolutely fixed. The drug should be titrated against the patient’s requirements.

Induction

Intravenous Route: The initial dose of ketamine administered intravenously may range from 1 mg/kg to 4.5 mg/kg (0.5 to 2 mg/lb). The average amount required to produce five to ten minutes of surgical anesthesia has been 2 mg/kg (1 mg/lb).

Alternatively, in adult patients an induction dose of 1 mg to 2 mg/kg intravenous ketamine at a rate of 0.5 mg/kg/min may be used for induction of anesthesia. In addition, diazepam in 2 mg to 5 mg doses, administered in a separate syringe over 60 seconds, may be used. In most cases, 15 mg of intravenous diazepam or less will suffice. The incidence of psychological manifestations during emergence, particularly dream-like observations and emergence delirium, may be reduced by this induction dosage program.

Note: The 100 mg/mL concentration of ketamine should not be injected intravenously without proper dilution. It is recommended the drug be diluted with an equal volume of either Sterile Water for Injection, Sodium Chloride Injection, 0.9% or Dextrose Injection, 5%.

Rate of Administration: It is recommended that ketamine be administered slowly (over a period of 60 seconds). More rapid administration may result in respiratory depression and enhanced pressor response.

Intramuscular Route: The initial dose of ketamine administered intramuscularly may range from 6.5 to 13 mg/kg (3 to 6 mg/lb). A dose of 10 mg/kg (5 mg/lb) will usually produce 12 to 25 minutes of surgical anesthesia.

Maintenance of Anesthesia

The maintenance dose should be adjusted according to the patient’s anesthetic needs and whether an additional anesthetic agent is employed.

Increments of one-half to the full induction dose may be repeated as needed for maintenance of anesthesia. However, it should be noted that purposeless and tonic-clonic movements of extremities may occur during the course of anesthesia. These movements do not imply a light plane and are not indicative of the need for additional doses of the anesthetic.

It should be recognized that the larger the total dose of ketamine administered, the longer will be the time to complete recovery.

Adult patients induced with ketamine augmented with intravenous diazepam may be maintained on ketamine given by slow microdrip infusion technique at a dose of 0.1 to 0.5 mg/minute, augmented with diazepam 2 to 5 mg administered intravenously as needed. In many cases 20 mg or less of intravenous diazepam total for combined induction and maintenance will suffice. However, slightly more diazepam may be required depending on the nature and duration of the operation, physical status of the patient, and other factors. The incidence of psychological manifestations during emergence, particularly dream-like observations and emergence delirium, may be reduced by this maintenance dosage program.

Dilution: To prepare a dilute solution containing 1 mg of ketamine per mL, aseptically transfer 10 mL (50 mg per mL vial) or 5 mL (100 mg per mL vial) to 500 mL of Dextrose Injection, 5% or Sodium Chloride Injection, 0.9% and mix well. The resultant solution will contain 1 mg of ketamine per mL.

The fluid requirements of the patient and duration of anesthesia must be considered when selecting the appropriate dilution of ketamine hydrochloride injection. If fluid restriction is required, ketamine hydrochloride injection can be added to a 250 mL infusion as described above to provide a ketamine concentration of 2 mg/mL.

Supplementary Agents

Ketamine is clinically compatible with the commonly used general and local anesthetic agents when an adequate respiratory exchange is maintained.

The regimen of a reduced dose of ketamine supplemented with diazepam can be used to produce balanced anesthesia by combination with other agents such as nitrous oxide and oxygen.

HOW SUPPLIED

Ketamine Hydrochloride Injection, USP is supplied as the hydrochloride in concentrations equivalent to ketamine base.

List | Container | Concentration | Fill | Quantity | NDC Number
2053 | Fliptop Vial | 50 mg/mL | 10 mL | Box of 10 | 54868-4399-0

Color of solution may vary from colorless to very slightly yellowish and may darken upon prolonged exposure to light. This darkening does not affect potency. Do not use if a precipitate appears.

Store at 20 to 25°C (68 to 77°F). [See USP Controlled Room Temperature.]

Protect from light.

ANIMAL PHARMACOLOGY AND TOXICOLOGY

Toxicity

The acute toxicity of ketamine has been studied in several species. In mature mice and rats, the intraperitoneal LD50 values are approximately 100 times the average human intravenous dose and approximately 20 times the average human intramuscular dose. A slightly higher acute toxicity observed in neonatal rats was not sufficiently elevated to suggest an increased hazard when used in children. Daily intravenous injections in rats of five times the average human intravenous dose and intramuscular injections in dogs at four times the average human intramuscular dose demonstrated excellent tolerance for as long as 6 weeks. Similarly, twice weekly anesthetic sessions of one, three, or six hours’ duration in monkeys over a four- to six-week period were well tolerated.

Interaction with other Drugs Commonly Used for Preanesthetic Medication

Large doses (three or more times the equivalent effective human dose) of morphine, meperidine, and atropine increased the depth and prolonged the duration of anesthesia produced by a standard anesthetizing dose of ketamine in Rhesus monkeys. The prolonged duration was not of sufficient magnitude to contraindicate the use of these drugs for preanesthetic medication in human clinical trials.

Blood Pressure

Blood pressure responses to ketamine vary with the laboratory species and experimental conditions. Blood pressure is increased in normotensive and renal hypertensive rats with and without adrenalectomy and under pentobarbital anesthesia.

Intravenous ketamine produces a fall in arterial blood pressure in the Rhesus monkey and a rise in arterial blood pressure in the dog. In this respect the dog mimics the cardiovascular effect observed in man. The pressor response to ketamine injected into intact, unanesthetized dogs is accompanied by a tachycardia, rise in cardiac output and a fall in total peripheral resistance. It causes a fall in perfusion pressure following a large dose injected into an artificially perfused vascular bed (dog hindquarters), and it has little or no potentiating effect upon vasoconstriction responses of epinephrine or norepinephrine. The pressor response to ketamine is reduced or blocked by chlorpromazine (central depressant and peripheral α-adrenergic blockade), by β-adrenergic blockade, and by ganglionic blockade. The tachycardia and increase in myocardial contractile force seen in intact animals does not appear in isolated hearts (Langendorff) at a concentration of 0.1 mg of ketamine nor in Starling dog heart-lung preparations at a ketamine concentration of 50 mg/kg of HLP. These observations support the hypothesis that the hypertension produced by ketamine is due to selective activation of central cardiac stimulating mechanisms leading to an increase in cardiac output. The dog myocardium is not sensitized to epinephrine and ketamine appears to have a weak antiarrhythmic activity.

Metabolic Disposition

Ketamine is rapidly absorbed following parenteral administration. Animal experiments indicated that ketamine was rapidly distributed into body tissues, with relatively high concentrations appearing in body fat, liver, lung, and brain; lower concentrations were found in the heart, skeletal muscle, and blood plasma. Placental transfer of the drug was found to occur in pregnant dogs and monkeys. No significant degree of binding to serum albumin was found with ketamine.

Balance studies in rats, dogs, and monkeys resulted in the recovery of 85% to 95% of the dose in the urine, mainly in the form of degradation products. Small amounts of drug were also excreted in the bile and feces. Balance studies with tritium-labeled ketamine in human subjects (1 mg/lb given intravenously) resulted in the mean recovery of 91% of the dose in the urine and 3% in the feces. Peak plasma levels averaged about 0.75 mcg/mL, and CSF levels were about 0.2 mcg/mL, 1 hour after dosing.

Ketamine undergoes N-demethylation and hydroxylation of the cyclohexanone ring, with the formation of water-soluble conjugates which are excreted in the urine. Further oxidation also occurs with the formation of a cyclohexanone derivative. The unconjugated N-demethylated metabolite was found to be less than one-sixth as potent as ketamine. The unconjugated demethyl cyclohexanone derivative was found to be less than one-tenth as potent as ketamine. Repeated doses of ketamine administered to animals did not produce any detectable increase in microsomal enzyme activity.

Reproduction

Male and female rats, when given five times the average human intravenous dose of ketamine for three consecutive days about one week before mating, had a reproductive performance equivalent to that of saline-injected controls. When given to pregnant rats and rabbits intramuscularly at twice the average human intramuscular dose during the respective periods of organogenesis, the litter characteristics were equivalent to those of saline-injected controls. A small group of rabbits was given a single large dose (six times the average human dose) of ketamine on Day 6 of pregnancy to simulate the effect of an excessive clinical dose around the period of nidation. The outcome of pregnancy was equivalent in control and treated groups.

To determine the effect of ketamine on the perinatal and postnatal period, pregnant rats were given twice the average human intramuscular dose during Days 18 to 21 of pregnancy. Litter characteristics at birth and through the weaning period were equivalent to those of the control animals. There was a slight increase in incidence of delayed parturition by one day in treated dams of this group. Three groups each of mated beagle bitches were given 2.5 times the average human intramuscular dose twice weekly for the three weeks of the first, second, and third trimesters of pregnancy, respectively, without the development of adverse effects in the pups.

©Hospira 2005 | EN-0861 | Printed in USA

HOSPIRA, INC., LAKE FOREST, IL 60045 USA

Additional barcode labeling by:
Physicians Total Care, Inc.
Tulsa, Oklahoma 74146

PRINCIPAL DISPLAY PANEL

Ketamine Hydrochloride Injection, USP

50 mg/mL

10 mL - box of 10

NDC 54868-4399-0